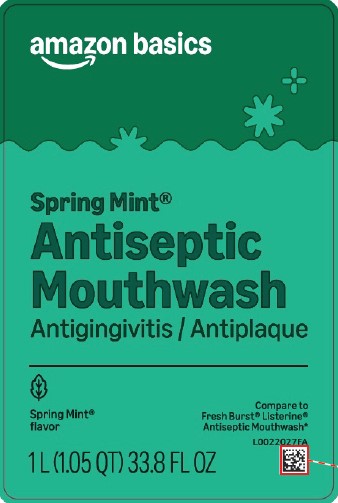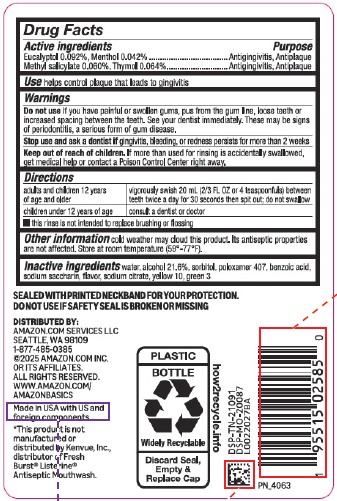 DRUG LABEL: Antiseptic Mouthrinse
NDC: 72288-072 | Form: MOUTHWASH
Manufacturer: Amazon.com Services LLC
Category: otc | Type: HUMAN OTC DRUG LABEL
Date: 20251222

ACTIVE INGREDIENTS: EUCALYPTOL 0.92 mg/1 mL; MENTHOL 0.42 mg/1 mL; METHYL SALICYLATE 0.6 mg/1 mL; THYMOL 0.64 mg/1 mL
INACTIVE INGREDIENTS: WATER; ALCOHOL; SORBITOL; POLOXAMER 407; BENZOIC ACID; SACCHARIN SODIUM; SODIUM CITRATE; D&C YELLOW NO. 10; FD&C GREEN NO. 3

Basics 072.003/072AN
Spring Mint Antiseptic Mouthrinse

Active ingredients

Eucalyptol 0.092%

Menthol 0.042%

Methyl sailcylate 0.060%

Thymol 0.064%

Purpose

Antigingivitis, Antiplaque

Use

helps control plaque that leads to gingivitis

Warnings

for this product

Do not use if

you have painful or swollen gums, pus from the gum line, loose teeth or increased spacing between the teeth. See your dentist immediately. These may be signs of periodontitis, a serious form of gum disease.

Stop use and ask a dentist if

gingivitis, bleeding, or redness persists for more than 2 weeks

Keep out of reach of children.

If more than used for rinsing is accidentally swallowed, get medical help or contact a Poison Control Center right away.

Directions

adults and children 12 years of age and older - vigorously swish 20 ml (2/3 FL OZ or 4 teaspoonfuls) between teeth twice a day for 30 seconds then spit out; do not swallow

children under 12 years of age - consult a dentist or doctor

- this rinse is not intended to replace brushing or flossing

Other information

cold weather may cloud this product. Its antiseptic propeties are not affected. Store at room temperature (59° -77° F).

Inactive ingredients

water, alcohol 21.6%, sorbitol, poloxamer 407, benzoic acid, sodium saccharin, flavor, sodium citrate, yellow 10, green 3

Tamper Evident Statement

SEALED WITH PRINTED NECKBAND FOR YOUR PROTECTION

DO NOT USE IF SAFETY SEAL IS BROKEN OR MISSING

Disclaimer

*This product is not manufactured or distributed by Kenvue, Inc., distributor of Fresh Burst® ListerineAntiseptic Mouthwash.

ADVERSE REACTION

Distributed by: Amazon.com Services, LLC

Seattle, WA 98109 1-877-485-0385

©2025 Amazon.com, Inc. or its affiliates.

All rights reserved.

www.amazon.com/amazonbasics

Made in USA with US and foreign components.

PLASTIC BOTTLE

Widely Recyclable

Discard Seal, Empty & Replace Cap

how2recycle.info

DSP-TN-21091

DSP-MO-20087

principal display panel

amazon basics

Spring Mint®

Antiseptic Mouthwash

Antigingivitis/Antiplaque

Spring Mint®Flavor

Compare to Fresh Burst® Listerine® Antiseptic Mouthwash*

1 L (1.05 QT) 33.8 FL OZ